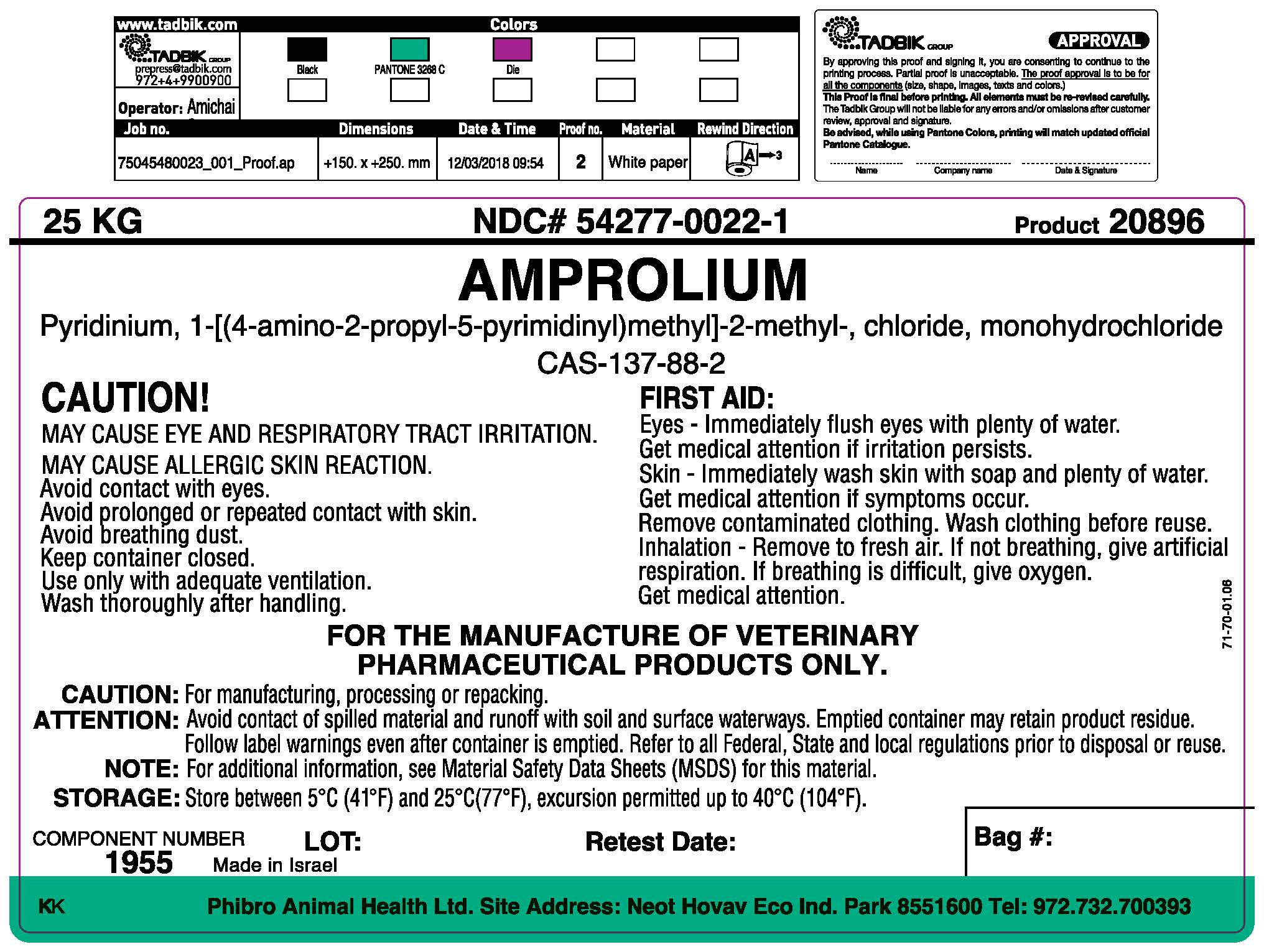 DRUG LABEL: AMPROLIUM
NDC: 54277-0022 | Form: POWDER
Manufacturer: Phibro Animal Health Ltd.
Category: other | Type: BULK INGREDIENT - ANIMAL DRUG
Date: 20220520

ACTIVE INGREDIENTS: AMPROLIUM 1 kg/1 kg

AMPROLIUM

Package Label/Prinicipal Display Panel

NDC # 54277-0022-1

Pyridinnium, 1-[(4-amino-2-propyl-5-pyridinyl)methyl]-2-methyl-, chloride, monohydrochloride

CAS- 137-88-2

Package Label/Prinicipal Display Panel

MAY CAUSE EYE AND RESPIRATORY TRACT IRRITATION

MAY CAUSE ALLERFGIC SKIN REACTION.

Avoid contact with eyes

Avoid prolonged or repeated contact with skin

Avoid breathing dust

Keep container closed

Use only with adequate ventilation.

Wash thoroughly after handling

FIRST AID:

Eye - Immediately flush eyes with plenty of water.

Get medical attention if irritation persists

Skin - Immediately wash skin with soap and plenty of water.

Get Medical attention if symptoms occur.

Remove contaminated clothing. Wash clothing before reuse.

Inhalation - Remove to fresh air. If not breathing, give artificial respiration. If breathing is difficult, give oxygen. Get medical attention.

FOR MANUFACTURING OF VETERINARY PHARMACEUTICAL PRODUCTS ONLY.

Caution: For manufacturing, processing or repacking. Attention: Avoid contact of spilled material and runoff with soil and surface waterways. Emptied container may retain product residue. Follow label warnings even after container is emptied. Refer to all Federal, State and local regulations prior to disposal or reuse. Note: For additional information, see Material Safety Data Sheets (MSDS) for this material.

Storage: Store between 5oC (41oF) and 25oC (77oF), excursions permitted up to 40oC (104oF).

COMPONENT NUMBER: 1955

Net Weight: 25 kg

Made in Israel

Phibro Animal Health Ltd.

Site Address: Neot Hovav Eco. Ind. Park

8551600

Component Number Lot Retest Date Bag #

Label

Add image transcription here...